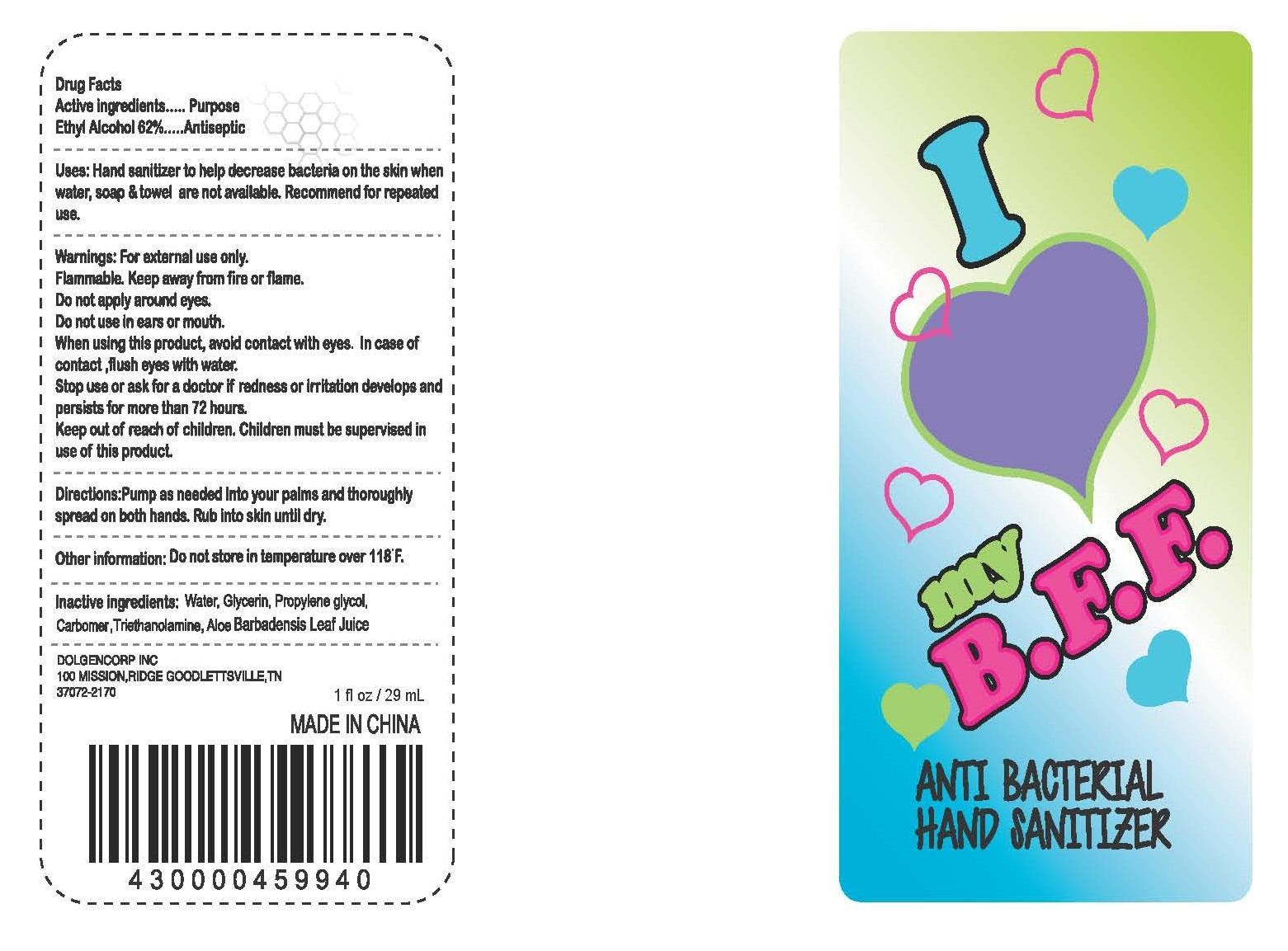 DRUG LABEL: ANTI BACTERIAL HAND SANITIZER
NDC: 55910-988 | Form: GEL
Manufacturer: Dolgencorp Inc
Category: otc | Type: HUMAN OTC DRUG LABEL
Date: 20140903

ACTIVE INGREDIENTS: Alcohol 62 mL/100 mL
INACTIVE INGREDIENTS: WATER; GLYCERIN; PROPYLENE GLYCOL; CARBOMER INTERPOLYMER TYPE A (ALLYL SUCROSE CROSSLINKED); TROLAMINE; ALOE VERA LEAF

Active ingredients

Ethyl Alcohol 62%

Purpose
Antiseptic

INDICATIONS AND USAGE

Uses: Hand sanitizer to help decrease bacteria on the skin when water, soap & towel are not available. Recommend for repeated use.

Warnings: For external use only.

Flammable. Keep away from fire or flame.

Do not apply around eyes.

Do not use in ears or mouth.
When using this product, avoid contact with eyes. In case of contact, flush eyes with water.

Stop use or ask for a doctor if redness or irritation develops and persists for more than 72 hours.

Keep out of reach of children. Children must be supervised in use of this product.

DOSAGE AND ADMINISTRATION

Directions: Pump as needed into your palms and thoroughly spread on both hands. Rub into skin until dry.

Other information: Do not store in temperature over 118 F.

INACTIVE INGREDIENT

INACTIVE INGREDIENTS:Water, Glycerin, Propylene Glycol, Carbomer, Triethanolamine, Aloe Barbadensis Leaf Juice